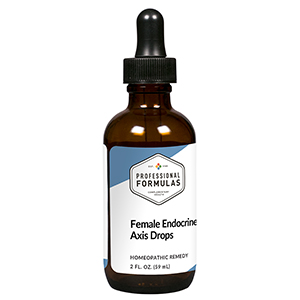 DRUG LABEL: Female Endocrine Axis Drops
NDC: 63083-5005 | Form: LIQUID
Manufacturer: Professional Complementary Health Formulas
Category: homeopathic | Type: HUMAN OTC DRUG LABEL
Date: 20190815

ACTIVE INGREDIENTS: CHASTE TREE FRUIT 3 [hp_X]/59 mL; BLACK COHOSH 3 [hp_X]/59 mL; SANGUINARIA CANADENSIS ROOT 3 [hp_X]/59 mL; SEPIA OFFICINALIS JUICE 3 [hp_X]/59 mL; ALETRIS FARINOSA ROOT 4 [hp_X]/59 mL; SUS SCROFA ADRENAL GLAND 6 [hp_X]/59 mL; CHAMAELIRIUM LUTEUM ROOT 6 [hp_X]/59 mL; STRYCHNOS IGNATII SEED 6 [hp_X]/59 mL; BOS TAURUS OVARY 6 [hp_X]/59 mL; BOS TAURUS PITUITARY GLAND, POSTERIOR 6 [hp_X]/59 mL; PULSATILLA MONTANA WHOLE 6 [hp_X]/59 mL; SUS SCROFA UTERUS 6 [hp_X]/59 mL; LACHESIS MUTA VENOM 8 [hp_X]/59 mL
INACTIVE INGREDIENTS: ALCOHOL; WATER

HFEA

ACTIVE INGREDIENTS

Agnus castus 3X
Cimicifuga racemosa 3X
Sanguinaria canadensis 3X
Sepia 3X
Aletris farinosa 4X
Adrenal 6X
Helonias dioica 6X
Ignatia amara 6X
Ovarian 6X
Pituitary 6X
Pulsatilla 6X
Uterus 6X
Lachesis mutus 8X

QUESTIONS

Professional Formulas

PO Box 2034 Lake Oswego, OR 97035

INDICATIONS

For the temporary relief of mild cramps, pain before menses, breast soreness, sadness, feeling tired or fatigued, mild back pain, flashes of heat, periodic nausea, nervousness, or lack of sexual desire.*

PURPOSE

*Claims based on traditional homeopathic practice, not accepted medical evidence. Not FDA evaluated.

WARNINGS

In case of overdose, get medical help or contact a poison control center right away.

Keep out of the reach of children.

PREGNANCY OR BREAST FEEDING

If pregnant or breastfeeding, ask a healthcare professional before use.

DIRECTIONS

Place drops under tongue 30 minutes before/after meals. Adults and children 12 years and over: Take 10 drops up to 3 times per day. Consult a physician for use in children under 12 years of age.

OTHER INFORMATION

Tamper resistant. If seal is broken, do not use. After opening, close container tightly and store at room temperature away from heat.

INACTIVE INGREDIENTS

20% ethanol, purified water.

LABEL

Est 1985

Professional Formulas

Complementary Health

Female Endocrine Axis Drops

Homeopathic Remedy

2 FL. OZ. (59 mL)